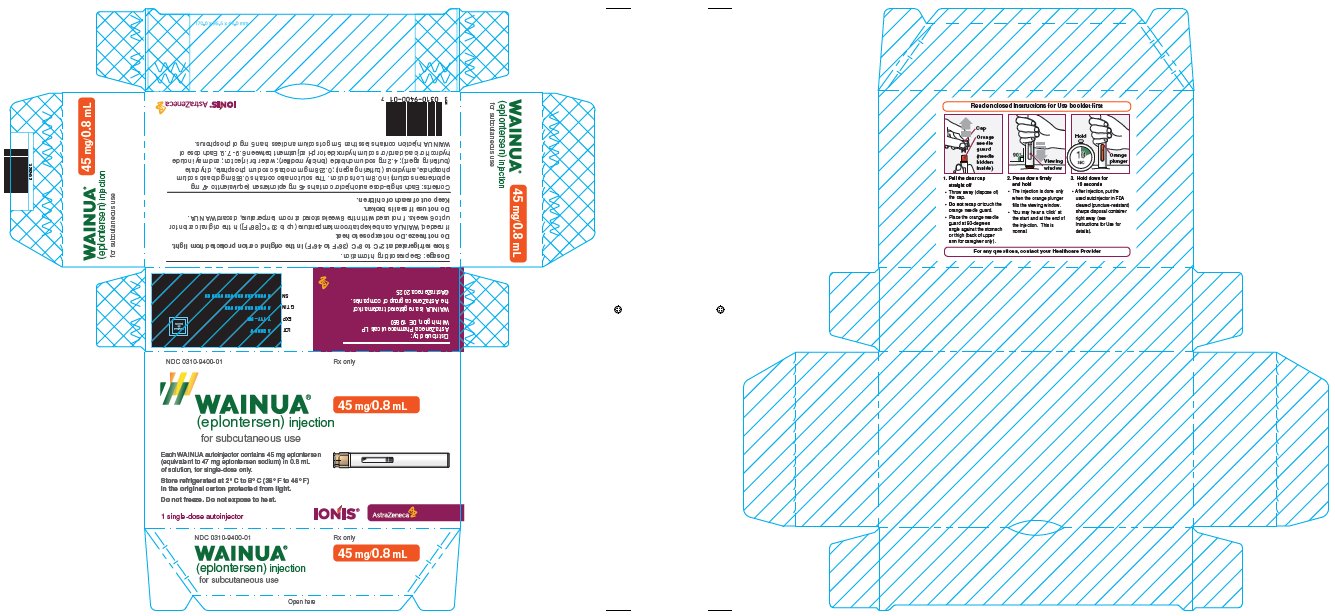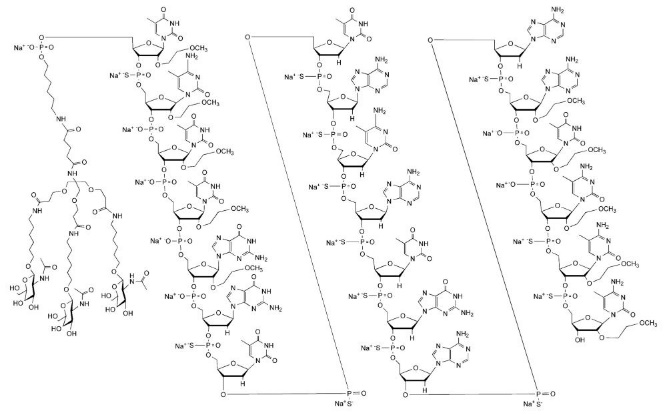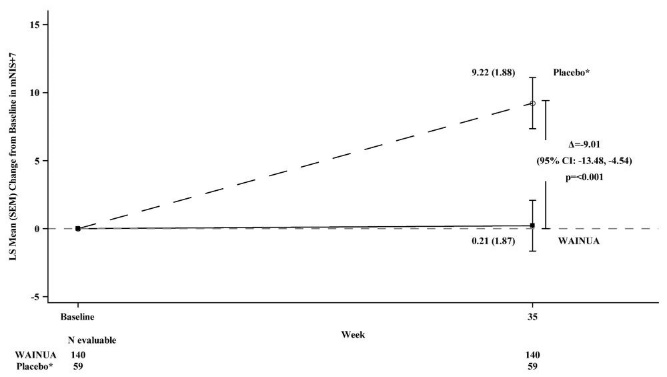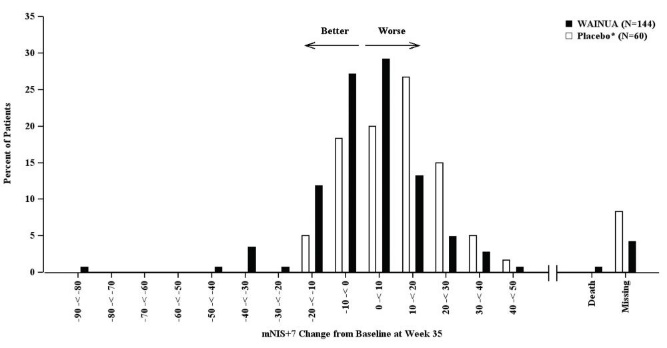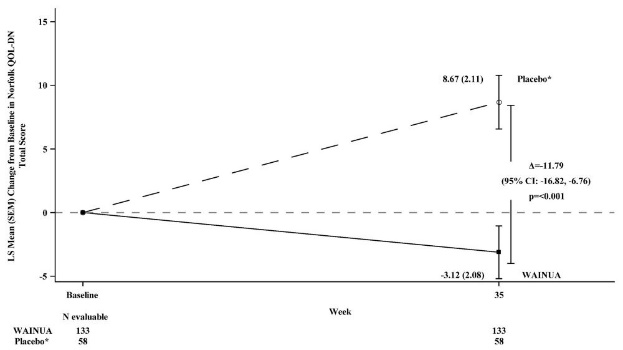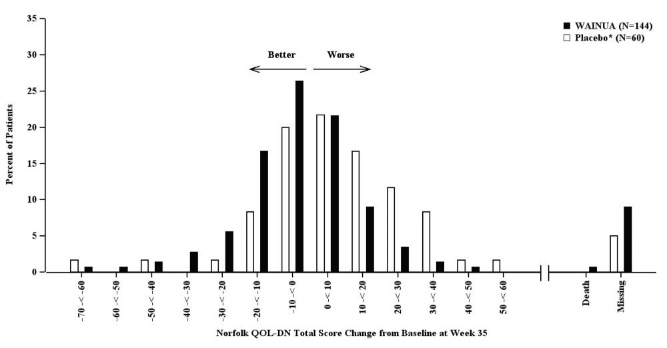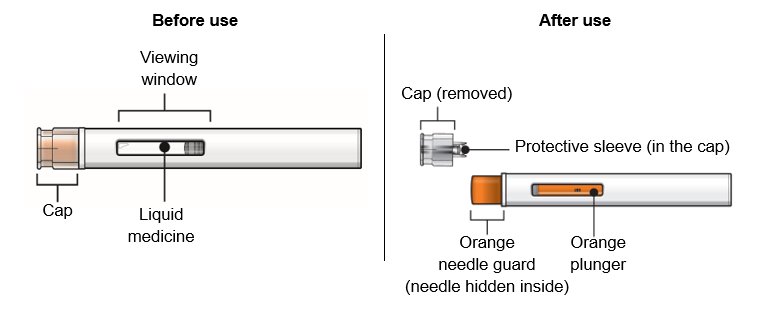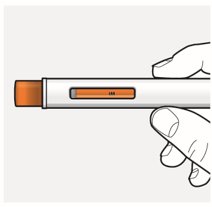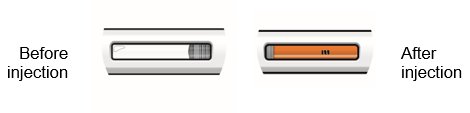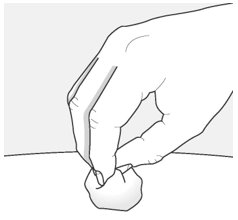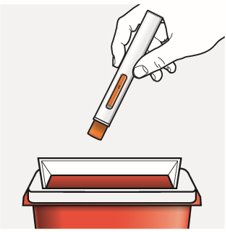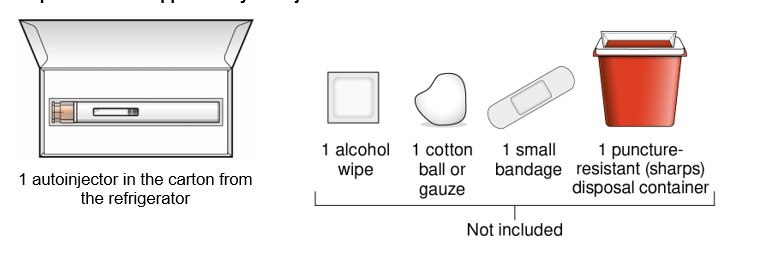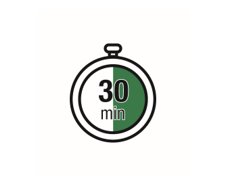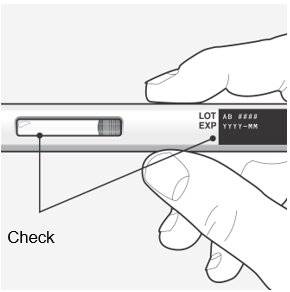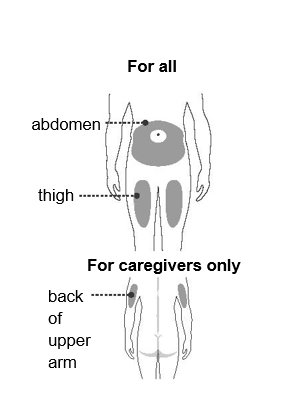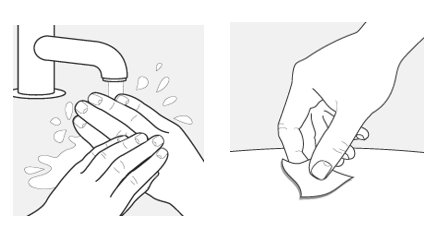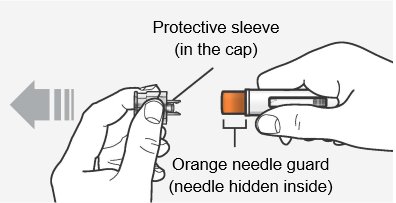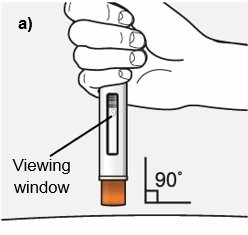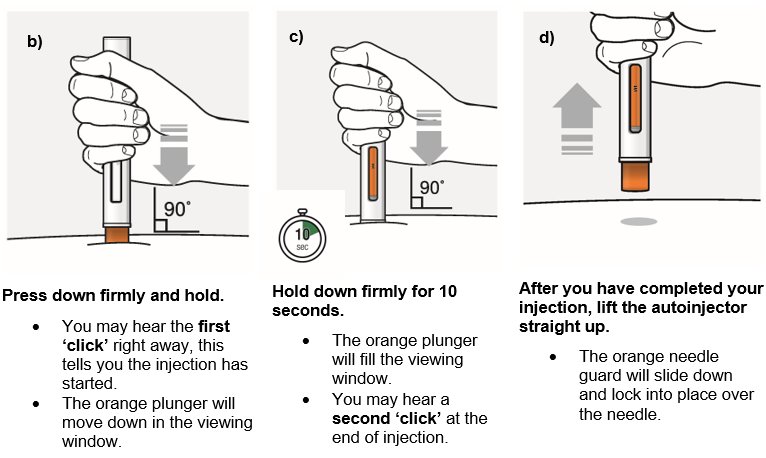 DRUG LABEL: WAINUA
NDC: 0310-9400 | Form: INJECTION, SOLUTION
Manufacturer: AstraZeneca Pharmaceuticals LP
Category: prescription | Type: HUMAN PRESCRIPTION DRUG LABEL
Date: 20251217

ACTIVE INGREDIENTS: EPLONTERSEN 45 mg/0.8 mL
INACTIVE INGREDIENTS: SODIUM PHOSPHATE, MONOBASIC, DIHYDRATE; SODIUM PHOSPHATE, DIBASIC, ANHYDROUS; SODIUM CHLORIDE; HYDROCHLORIC ACID; SODIUM HYDROXIDE; WATER

HIGHLIGHTS OF PRESCRIBING INFORMATION

These highlights do not include all the information needed to use WAINUA safely and effectively. See full prescribing information for WAINUA.
WAINUA® (eplontersen) injection, for subcutaneous use
Initial U.S. Approval: 2023

1 INDICATIONS AND USAGE

WAINUA is a transthyretin-directed antisense oligonucleotide indicated for the treatment of the polyneuropathy of hereditary transthyretin-mediated amyloidosis in adults. (1)

2 DOSAGE AND ADMINISTRATION

- The recommended dosage of WAINUA is 45 mg administered by subcutaneous injection once monthly. (2.1)
- Administer WAINUA into the abdomen or upper thigh region; the back of the upper arm can be used if a healthcare provider or caregiver administers the injection. (2.2)

3 DOSAGE FORMS AND STRENGTHS

Injection: 45 mg/0.8 mL in a single-dose autoinjector. (3)

4 CONTRAINDICATIONS

None. (4)

5 WARNINGS AND PRECAUTIONS

Reduced Serum Vitamin A Levels and Recommended Supplementation: Supplement with the recommended daily allowance of vitamin A. Refer to an ophthalmologist if ocular symptoms suggestive of vitamin A deficiency occur. (5.1)

6 ADVERSE REACTIONS

Most common adverse reactions (that occurred in at least 9% of patients treated with WAINUA) were vitamin A decreased and vomiting. (6.1)

To report SUSPECTED ADVERSE REACTIONS, contact AstraZeneca at 1-800-236-9933 or FDA at 1-800-FDA-1088 or www.fda.gov/medwatch.

FULL PRESCRIBING INFORMATION

1 INDICATIONS AND USAGE

WAINUA is indicated for the treatment of the polyneuropathy of hereditary transthyretin-mediated amyloidosis in adults.

2 DOSAGE AND ADMINISTRATION

2.1 Recommended Dosage

The recommended dosage of WAINUA is 45 mg administered by subcutaneous injection once monthly [see Dosage and Administration (2.2)].

Missed Dose

Administer WAINUA as soon as possible after a missed dose. Resume dosing at monthly intervals from the date of the most recently administered dose.

2.2 Administration Instructions

Prior to initiation, train patients and/or caregivers on proper preparation and administration of WAINUA [see Instructions for Use].

Remove the single-dose autoinjector from the refrigerator 30 minutes prior to the injection and allow to warm to room temperature. Do not use other warming methods.

Inspect WAINUA visually for particulate matter and discoloration prior to administration. The solution should appear colorless to yellow. Do not use if cloudiness, particulate matter, or discoloration is observed prior to administration.

Administer WAINUA as a subcutaneous injection into the abdomen or upper thigh region. The back of the upper arm can also be used as an injection site if a healthcare provider or caregiver administers the injection.

3 DOSAGE FORMS AND STRENGTHS

Injection: 45 mg/0.8 mL of eplontersen as a clear, colorless-to-yellow solution in a single-dose autoinjector.

4 CONTRAINDICATIONS

None.

5 WARNINGS AND PRECAUTIONS

5.1 Reduced Serum Vitamin A Levels and Recommended Supplementation

WAINUA treatment leads to a decrease in serum vitamin A levels [see Adverse Reactions (6.1), Use in Specific Populations (8.1), and Clinical Pharmacology (12.2)].

Supplementation at the recommended daily allowance of vitamin A is advised for patients taking WAINUA. Higher doses than the recommended daily allowance of vitamin A should not be given to try to achieve normal serum vitamin A levels during treatment with WAINUA, as serum vitamin A levels do not reflect the total vitamin A in the body.

Patients should be referred to an ophthalmologist if they develop ocular symptoms suggestive of vitamin A deficiency (e.g., night blindness, dry eyes).

6 ADVERSE REACTIONS

The following clinically significant adverse reactions are discussed in greater detail in other sections of the labeling:

- Reduced Serum Vitamin A Levels and Recommended Supplementation [see Warnings and Precautions (5.1)].

6.1 Clinical Trials Experience

Because clinical trials are conducted under widely varying conditions, adverse reaction rates observed in the clinical trials of WAINUA cannot be directly compared to rates in the clinical trials of another drug and may not reflect the rates observed in practice.

In Study 1 [see Clinical Studies (14)], a total of 144 patients with polyneuropathy caused by hereditary transthyretin-mediated amyloidosis (hATTR amyloidosis) were randomized to WAINUA and received at least one dose of WAINUA. Of these, 141 patients received at least 6 months of treatment and 107 patients received at least 12 months of treatment. The mean duration of treatment was 15 months (range: 1.9 to 19.4 months). The median patient age at baseline was 52 years and 69% of the patients were male. Seventy-eight percent of patients treated with WAINUA were White, 15% were Asian, 4% were Black, 2% were reported as other races, and <1% were multiple races. Fifty-nine percent of patients had the Val30Met variant in the transthyretin gene; the remaining patients had one of 19 other variants. At baseline, 80% of patients were in Stage 1 of the disease and 20% were in Stage 2 with a mean duration from polyneuropathy diagnosis of 47 months. The mean duration from onset of polyneuropathy symptoms was 68 months.

Table 1 lists the adverse reactions that occurred in at least 5% of patients treated with WAINUA in Study 1.

Table 1: Adverse Reactions Reported in at least 5% of Patients Treated with WAINUA (Study 1)
Adverse Reaction | WAINUA; N=144; %
Vitamin A decreased [Vitamin A decreased includes vitamin A deficiency and vitamin A decrease.] | 15
Vomiting | 9
Proteinuria | 8
Injection site reactions [Injection site reactions includes erythema, pain, and pruritis.] | 7
Blurred vision | 6
Cataract | 6

Three serious adverse reactions of atrioventricular (AV) heart block (2%) occurred in WAINUA-treated patients, including 1 case of complete AV block.

Laboratory Tests

Vitamin A Decrease

In Study 1, patients were instructed to take the recommended daily allowance of vitamin A [see Warnings and Precautions (5.1)]. All patients treated with WAINUA had normal vitamin A levels at baseline, 95% of patients developed low vitamin A levels during the study. In some cases, the decreased vitamin A level was reported as an adverse reaction.

8 USE IN SPECIFIC POPULATIONS

8.1 Pregnancy

Risk Summary

There are no available data on WAINUA use in pregnant women to inform drug-associated risk of adverse developmental outcomes. WAINUA treatment leads to a decrease in serum vitamin A levels, and vitamin A supplementation is advised for patients taking WAINUA. Vitamin A is essential for normal embryofetal development; however, excessive levels of vitamin A are associated with adverse developmental effects. The effect of vitamin A supplementation on the fetus in the setting of a reduction in maternal serum TTR caused by WAINUA administration is unknown [see Clinical Pharmacology (12.2) and Warnings and Precautions (5.1)].

No adverse developmental effects were observed when eplontersen or a mouse-specific surrogate was administered to mice prior to mating and continuing throughout organogenesis [see Animal Data].

In the U.S. general population, the estimated background risk of major birth defects and miscarriage in clinically recognized pregnancies is 2-4% and 15-20%, respectively. The background risk of major birth defects and miscarriage for the indicated population is unknown.

Data

Animal Data

Subcutaneous administration of eplontersen (0, 5, 25, or 75 mg/kg) or a mouse-specific surrogate (25 mg/kg) to male and female mice weekly prior to and during mating and administration continued every other day in females throughout the period of organogenesis resulted in no adverse effects on embryofetal development.

8.2 Lactation

Risk Summary

There is no information regarding the presence of eplontersen in human milk, the effects on the breast-fed infant, or the effects on milk production. The developmental and health benefits of breastfeeding should be considered along with the mother’s clinical need for WAINUA and any potential adverse effects on the breast-fed infant from WAINUA or from the underlying maternal condition.

8.4 Pediatric Use

Safety and effectiveness in pediatric patients have not been established.

8.5 Geriatric Use

No dose adjustment is required in patients ≥65 years of age [see Clinical Pharmacology (12.3)]. In Study 1 [see Clinical Studies (14)], 44 (31%) patients were 65 to 74 years of age, and 8 (5.6%) patients were ≥75 years of age. No overall differences in safety or effectiveness were observed between these patients and younger adult patients, but greater sensitivity of some older individuals cannot be ruled out.

8.6 Renal Impairment

No dose adjustment is necessary in patients with mild to moderate renal impairment (estimated glomerular filtration rate [eGFR] ≥30 to <90 mL/min/1.73 m^2) [see Clinical Pharmacology (12.3)].

WAINUA has not been studied in patients with severe renal impairment or end-stage renal disease.

8.7 Hepatic Impairment

No dose adjustment is necessary in patients with mild hepatic impairment (total bilirubin ≤1 x ULN and AST >1 x ULN, or total bilirubin >1.0 to 1.5 x ULN and any AST) [see Clinical Pharmacology (12.3)].

WAINUA has not been studied in patients with moderate or severe hepatic impairment.

11 DESCRIPTION

Eplontersen is a transthyretin-directed antisense oligonucleotide (ASO), covalently linked to a ligand containing three N-acetyl galactosamine (GalNAc) residues to enable delivery of the ASO to hepatocytes.

WAINUA contains eplontersen sodium as the active ingredient. Eplontersen sodium is a white to yellow solid and it is freely soluble in water and in phosphate buffer. The molecular formula of eplontersen sodium is C296H417N77O156P20S13Na20 and the molecular weight is 9046.1 daltons. The chemical name of eplontersen sodium is DNA, d([2′-O-(2-methoxyethyl)]m5rU-sp-[2′-O-(2-methoxyethyl)]m5rC-[2′-O-(2-methoxyethyl)]m5rU-[2′-O-(2-methoxyethyl)]m5rU-[2′-O-(2-methoxyethyl)]rG-G-sp-T-sp-T-sp-A-sp-m5C-sp-A-sp-T-sp-G-sp-A-sp-A-sp-[2′-O-(2-methoxyethyl)]rA-[2′-O-(2-methoxyethyl)]m5rU-[2′-O-(2-methoxyethyl)]m5rC-sp-[2′-O-(2-methoxyethyl)]m5rC-sp-[2′-O-(2-methoxyethyl)]m5rC), 5′-[26-[[2-(acetylamino)-2-deoxy-β-D-galactopyranosyl]oxy]-14,14-bis[[3-[[6-[[2-(acetylamino)-2-deoxy-β-D-galactopyranosyl]oxy]hexyl]amino]-3-oxopropoxy]methyl]-8,12,19-trioxo-16-oxa-7,13,20-triazahexacos-1-yl hydrogen phosphate], sodium salt (1:20).

The structure of eplontersen sodium is presented below:

WAINUA is a sterile, preservative-free, aqueous solution for subcutaneous injection. Each single-dose autoinjector contains 45 mg eplontersen (equivalent to 47 mg eplontersen sodium) in 0.8 mL of solution. The solution also contains 0.868 mg dibasic sodium phosphate, anhydrous (buffering agent); 0.238 mg monobasic sodium phosphate, dihydrate (buffering agent); 4.2 mg sodium chloride (tonicity modifier); water for injection; and may include hydrochloric acid and/or sodium hydroxide for pH adjustment between 6.9 - 7.9. Each dose of WAINUA injection contains less than 5 mg of sodium and less than 5 mg of phosphorus.

12 CLINICAL PHARMACOLOGY

12.1 Mechanism of Action

Eplontersen is an antisense oligonucleotide-GalNAc conjugate that causes degradation of mutant and wild-type TTR mRNA through binding to the TTR mRNA, which results in a reduction of serum TTR protein and TTR protein deposits in tissues.

12.2 Pharmacodynamics

In Study 1 [see Clinical Studies (14)], following administration of the recommended WAINUA dosage every 4 weeks to patients with hATTR amyloidosis, a decrease in serum TTR levels was observed at the first assessment and the (least square) mean serum TTR at Week 35 was reduced by 81% from baseline. Similar TTR reductions were observed across subgroups including Val30Met variant status, body weight, sex, age, or race.

Eplontersen also reduced the mean steady state serum vitamin A by 71% by Week 37 [see Warnings and Precautions (5.1)].

Cardiac Electrophysiology

At a dose 2.7-times the maximum recommended dose for WAINUA, clinically significant QTc interval prolongation was not observed.

12.3 Pharmacokinetics

The pharmacokinetic (PK) properties of WAINUA were evaluated following subcutaneous administration of single and multiple doses (once every 4 weeks) in healthy subjects and multiple doses (once every 4 weeks) in patients with hATTR amyloidosis.

Eplontersen Cmax and AUC showed a slightly greater than dose-proportional increase following single subcutaneous doses ranging from 45 to 120 mg (i.e., 1- to 2.7-times the recommended dose) in healthy volunteers.

Population estimates (mean ± SD) of steady state maximum concentrations (Cmax), and area under the curve (AUCτ) were 283 ± 152 ng/mL, and 2190 ± 689 ng/mL, respectively, following 45 mg monthly dosing in patients with hATTR amyloidosis. No accumulation of eplontersen Cmax and AUC was observed in repeated dosing (once every 4 weeks).

Absorption

Following subcutaneous administration, eplontersen is absorbed with the time to maximum plasma concentrations of approximately 2 hours, based on population estimates.

Distribution

Eplontersen is expected to distribute primarily to the liver and kidney cortex after subcutaneous dosing. Eplontersen is bound to human plasma proteins (>98%) in vitro. The population estimate for the apparent central volume of distribution is 12 L and the apparent peripheral volume of distribution is 11,100 L.

Elimination

The terminal elimination half-life is approximately 3 weeks.

Metabolism

Eplontersen is metabolized by endo- and exonucleases to short oligonucleotide fragments of varying sizes within the liver.

Excretion

The mean fraction of unchanged ASO eliminated in urine was less than 1% of the administered dose within 24 hours.

Specific Populations

Population pharmacokinetic and pharmacodynamic analysis showed no clinically meaningful differences in the pharmacokinetics or pharmacodynamics of eplontersen based on age, body weight, sex, race, Val30Met variant status, mild and moderate renal impairment (eGFR≥30 to <90 mL/min), or mild hepatic impairment (total bilirubin ≤1 x ULN and AST > 1 x ULN, or total bilirubin >1.0 to 1.5 x ULN and any AST). Eplontersen has not been studied in patients with severe renal impairment, end-stage renal disease, or in patients with moderate to severe hepatic impairment, or in patients with prior liver transplant.

Drug Interaction Studies

No clinical drug-drug interaction studies have been performed with eplontersen. In vitro studies show that eplontersen is not a substrate or inhibitor of transporters, does not interact with highly plasma protein bound drugs, and is not an inhibitor or inducer of cytochrome P450 (CYP) enzymes. Oligonucleotide therapeutics, including eplontersen, are not typically substrates of CYP enzymes. Therefore, eplontersen is not expected to cause or be affected by drug-drug interactions mediated through drug transporters, plasma protein binding or CYP enzymes.

12.6 Immunogenicity

The observed incidence of anti-drug antibodies (ADAs) is highly dependent on the sensitivity and specificity of the assay. Differences in assay methods preclude meaningful comparisons of the incidence of ADAs in the study described below with the incidence of anti-drug antibodies in other studies, including those of eplontersen.

In Study 1, with duration of treatment up to 85 weeks (mean treatment duration of 445 days (63.2 weeks), range: 57 to 582 days), 53 out of 144 (37%) patients developed treatment-emergent ADAs during treatment with WAINUA. The presence of ADAs did not affect eplontersen plasma Cmax or AUC, but increased Ctrough. Although anti-drug antibody development was not found to affect the pharmacokinetics, pharmacodynamics, safety, or efficacy of WAINUA in these patients, the available data are too limited to make definitive conclusions.

13 NONCLINICAL TOXICOLOGY

13.1 Carcinogenesis, Mutagenesis, Impairment of Fertility

Carcinogenesis

In a 26-week carcinogenicity study in male and female Tg.rasH2 mice, subcutaneous administration of eplontersen (0, 250, 500, or 1500 mg/kg) monthly for 26 weeks resulted in no increase in neoplasms.

Mutagenesis

Eplontersen was negative for genotoxicity in in vitro (bacterial reverse mutation, chromosomal aberration in Chinese hamster lung cells) and in vivo (mouse bone marrow micronucleus) assays.

Impairment of Fertility

Subcutaneous administration of eplontersen (0, 5, 25, or 75 mg/kg) or a mouse-specific surrogate (25 mg/kg) to male and female mice weekly prior to and during mating and continuing in females throughout the period of organogenesis resulted in no adverse effects on fertility.

14 CLINICAL STUDIES

The efficacy of WAINUA was demonstrated in a randomized, open-label, multicenter clinical trial in adult patients with polyneuropathy caused by hATTR amyloidosis (Study 1; NCT04136184). Patients were randomized in a 6:1 ratio to receive either 45 mg of WAINUA once every 4 weeks (N=144), or 284 mg of inotersen once per week (N=24), respectively, as subcutaneous injections. Ninety-seven percent of WAINUA-treated patients and 83% of inotersen-treated patients completed at least 35 weeks of the assigned treatment.

Efficacy assessments were based on a comparison of the WAINUA arm of Study 1 with an external placebo group (N=60) in another study (NCT01737398) composed of a comparable population of adult patients with polyneuropathy caused by hATTR amyloidosis.

The efficacy endpoints were the change from baseline to Week 35 in the modified Neuropathy Impairment Scale+7 (mNIS+7) composite score and the change from baseline to Week 35 in the Norfolk Quality of Life-Diabetic Neuropathy (QoL-DN) total score.

The mNIS+7 is an objective assessment of neuropathy and comprises the neuropathy impairment score (NIS) and Modified +7 composite scores. In the version of the mNIS+7 used in the trial, the NIS objectively measures deficits in cranial nerve function, muscle strength, reflexes, and sensations, and the Modified +7 assesses heart rate response to deep breathing, quantitative sensory testing (touch-pressure and heat-pain), and peripheral nerve electrophysiology. The validated version of the mNIS+7 score used in the trial has a range of -22.3 to 346.3 points, with higher scores representing a greater severity of disease.

The clinical meaningfulness of effects on the mNIS+7 was assessed by the change from baseline to Week 35 in Norfolk Quality of Life-Diabetic Neuropathy (QoL-DN) total score. The Norfolk QoL-DN scale is a patient-reported assessment that evaluates the subjective experience of neuropathy in the following domains: physical functioning/large fiber neuropathy, activities of daily living, symptoms, small fiber neuropathy, and autonomic neuropathy. The version of the Norfolk QoL-DN that was used in the trial has a range from -4 to 136 points, with higher scores representing greater impairment.

Treatment with WAINUA resulted in statistically significant improvements in the mNIS+7 and the Norfolk QoL-DN total scores, compared to the external placebo control (p<0.001) at Week 35 (Table 2, Figures 1 and 3). The distributions of changes in mNIS+7 and Norfolk QoL-DN scores from baseline to Week 35 by percent of patients in each category are shown in Figure 2 and Figure 4, respectively.

Table 2: Clinical Efficacy Results (Comparison of WAINUA Treatment in Study 1 to an External Placebo Control [External placebo group from another randomized controlled trial (NCT01737398).])
Endpoint | Baseline, Mean (SD) |  | Change from Baseline to Week 35, LS Mean (SEM) |  | Treatment Difference LS Mean; (95% CI) | p-value
Endpoint | WAINUA N = 140; (Study 1) | Placebo N = 59 (NCT01737398) | WAINUA (Study 1) | Placebo (NCT01737398) | WAINUA- Placebo | p-value
mNIS+7 [Based on an analysis of covariance (ANCOVA) model. Patients with a missing mNIS+7 or Norfolk QoL-DN at Week 35 had values multiply imputed using an imputation model.] | 79.6; (42.3) | 74.1 (39.0) | 0.2 (1.9) | 9.2 (1.9) | -9.0 (-13.5, -4.5) | <0.001
Norfolk QOL-DN | 43.5; (26.3) | 48.6 (27.0) | -3.1 (2.1) | 8.7 (2.1) | -11.8 (-16.8, -6.8) | <0.001
CI = confidence interval; LS mean = least squares mean; mNIS = modified Neuropathy Impairment Score; QoL-DN = Quality of Life-Diabetic Neuropathy; SD = standard deviation; SEM = standard error of the mean.

Figure 1: Change from Baseline in mNIS+7 at Week 35 (Comparison of WAINUA Treatment in Study 1 to an External Placebo Control*)

* External placebo group from another randomized controlled trial (NCT01737398).
Based on an analysis of covariance (ANCOVA) model. Patients with a missing mNIS+7 at Week 35 had values multiply imputed using an imputation model.

Figure 2: Histogram of mNIS+7 Change from Baseline at Week 35 (Comparison of WAINUA Treatment in Study 1 to an External Placebo Control*)

* External placebo group from another randomized controlled trial (NCT01737398).
Categories are mutually exclusive; patients who died before Week 35 are summarized in the Death category only; missing mNIS+7 values not imputed; patients with missing values at Week 35 presented in the Missing category.

Figure 3: Change from Baseline in Norfolk QoL-DN Total Score at Week 35 (Comparison of WAINUA Treatment in Study 1 to an External Placebo Control*)

* External placebo group from another randomized controlled trial (NCT01737398).
Based on an analysis of covariance (ANCOVA) model. Patients with a missing Norfolk QoL-DN at Week 35 had values multiply imputed using an imputation model.

Figure 4: Histogram of Norfolk QoL-DN Total Score Change from Baseline at Week 35 (Comparison of WAINUA Treatment in Study 1 to an External Placebo Control*)

* External placebo group from another randomized controlled trial (NCT01737398).
Categories are mutually exclusive; patients who died before Week 35 are summarized in the Death category only; missing Norfolk QoL-DN values not imputed; patients with missing values at Week 35 presented in the Missing category.

Patients receiving WAINUA experienced similar improvements relative to those in the external placebo in mNIS+7, and Norfolk QoL-DN score across subgroups including age, sex, race, region, Val30Met variant status, and disease stage.

16 HOW SUPPLIED/STORAGE AND HANDLING

16.1 How Supplied

WAINUA injection is a sterile, preservative-free, clear, colorless to yellow solution supplied in a single-dose autoinjector. Each autoinjector of WAINUA is filled to deliver 0.8 mL of solution containing 45 mg of eplontersen.

WAINUA is available in cartons containing one 45 mg single-dose autoinjector each.

The NDC is: 0310-9400-01.

16.2 Storage and Handling

Store refrigerated at 2°C to 8°C (36°F to 46°F) in the original carton protected from light.

If needed, WAINUA can be kept at room temperature (up to 30°C [86°F]) in the original carton for up to 6 weeks. If not used within the 6 weeks stored at room temperature, discard WAINUA.

Do not freeze. Do not expose to heat.

17 PATIENT COUNSELING INFORMATION

Advise the patient to read the FDA-approved patient labeling (Patient Information and Instructions for Use).

Recommended Vitamin A Supplementation

Inform patients that WAINUA treatment leads to a decrease in vitamin A levels measured in the serum. Instruct patients to take the recommended daily allowance of vitamin A. Advise patients to contact their healthcare provider if they experience ocular symptoms suggestive of vitamin A deficiency (e.g., night blindness, dry eyes) and refer them to an ophthalmologist if they develop these symptoms [see Warnings and Precautions (5.1)].

Pregnancy

Instruct patients that if they are pregnant or plan to become pregnant while taking WAINUA they should inform their healthcare provider. Advise patients of the potential risk to the fetus, including that WAINUA treatment leads to a decrease in serum vitamin A levels [see Use in Special Populations (8.1)].

Distributed by: AstraZeneca Pharmaceuticals LP, Wilmington, DE 19850

©AstraZeneca 2025

PATIENT INFORMATION

WAINUA [way-noo’-ah]

(eplontersen)

injection, for subcutaneous use

What is WAINUA?

WAINUA is a prescription medicine used to treat adults with polyneuropathy of hereditary transthyretin-mediated amyloidosis.

It is not known if WAINUA is safe and effective in children.

Before you take WAINUA, tell your healthcare provider if you:

- are pregnant or plan to become pregnant. It is not known if WAINUA can harm your unborn baby. Changes in vitamin A levels and vitamin A supplementation related to use of WAINUA may harm your unborn baby. Tell your healthcare provider if you become pregnant or think you may be pregnant while taking WAINUA.
- are breastfeeding or plan to breastfeed. It is not known if WAINUA can pass into your breast milk or harm your baby. Talk with your healthcare provider about the best way to feed your baby while you are using WAINUA.

Tell your healthcare provider about all the medicines you take, including prescription and over-the-counter medicines, vitamins, and herbal supplements.

Especially tell your healthcare provider if you take:

- Vitamin A or beta-carotene supplements.

Ask your healthcare provider or pharmacist if you are not sure if you take any of these medicines. Know the medicines you take. Keep a list of them to show your healthcare provider or pharmacist when you get a new medicine.

How should I take WAINUA?

- Read the detailed Instructions for Use that come with your WAINUA single-dose autoinjector.
- Your healthcare provider will show you or your caregiver how to inject WAINUA the first time.
- If you or your caregiver have any questions, ask your healthcare provider.
- WAINUA is injected under your skin (subcutaneously) in your stomach area (abdomen), or the front of your upper legs (thighs) by you or a caregiver. A caregiver may also give you an injection of WAINUA in the outer area of your upper arm.
- Follow your healthcare provider’s instructions on when to inject WAINUA.
- WAINUA should be injected 1 time on the same day of each month.
- If you miss a dose, take the missed dose as soon as possible. Then inject WAINUA 1 month from the date of your last dose to get back on a monthly dosing schedule. If you have questions about your schedule, ask your healthcare provider.

What are the possible side effects of WAINUA?

WAINUA may cause side effects, including:

- Low vitamin A level. Low vitamin A level is a serious, but common side effect of treatment with WAINUA. Your healthcare provider should tell you to take vitamin A supplements while using WAINUA. Do not take more than the amount of vitamin A your healthcare provider has recommended. Call your healthcare provider if you develop eye problems such as difficulty seeing at night or in low lit areas (night blindness), or dry eyes. If you develop eye problems while receiving treatment with WAINUA, your healthcare provider should send you to see an eye doctor (ophthalmologist).

The most common side effects of WAINUA include decreased vitamin A and vomiting.

These are not all of the possible side effects of WAINUA. For more information, ask your healthcare provider or pharmacist.

Call your doctor for medical advice about side effects. You may report side effects to FDA at 1‑800-FDA-1088.

How should I store WAINUA?

- Store WAINUA in the refrigerator between 36°F to 46°F (2°C to 8°C) in the original carton.
- WAINUA can also be kept at room temperature that is no higher than 86°F (30°C) in the original carton for up to 6 weeks.
- Do not let WAINUA reach temperatures above 86°F (30°C).
- If you do not use WAINUA kept at room temperature within 6 weeks, throw it away.
- Do not freeze.
- Do not expose WAINUA to heat.
- Protect from light.

Keep WAINUA and all medicines out of the reach of children.

General information about the safe and effective use of WAINUA.

Medicines are sometimes prescribed for purposes other than those listed in a Patient Information Leaflet. Do not use WAINUA for a condition for which it was not prescribed. Do not give WAINUA to other people, even if they have the same symptoms you have. It may harm them. You can ask your pharmacist or healthcare provider for information about WAINUA that is written for health professionals.

What are the ingredients in WAINUA?

Active ingredient: eplontersen sodium.

Inactive ingredients: dibasic sodium phosphate, anhydrous; monobasic sodium phosphate, dihydrate; sodium chloride; water for injection, and may include hydrochloric acid and sodium hydroxide for pH adjustment.

Distributed by: AstraZeneca Pharmaceuticals LP, Wilmington, DE 19850

©AstraZeneca 2023

For more information, go to https://www.wainua.com or call 1-800-236-9933. If you still have questions, contact your healthcare provider.

This Patient Information has been approved by the U.S. Food and Drug Administration Approved: 12/2023

INSTRUCTIONS FOR USE

WAINUA [way-noo’-ah]
(eplontersen)
injection, for subcutaneous use
Single-dose autoinjector

45 mg/0.8 mL

This Instructions for Use contains information on how to inject WAINUA using the autoinjector.

Read this Instructions for Use before you start using the WAINUA autoinjector and each time you get a refill. There may be new information. This information does not take the place of talking to your healthcare provider about your medical condition and your treatment.

Your healthcare provider should show you or your caregiver how to use the autoinjector the right way. If you or your caregiver have any questions, talk to your healthcare provider.

Important information you need to know before using WAINUA
Keep your autoinjector and all medicines out of the sight and reach of children.

- WAINUA is for use by injection under the skin (subcutaneous use) only.
- Each WAINUA autoinjector contains 1 dose and can only be used 1 time.
- Do not share your autoinjector with anyone.
- Do not use the autoinjector if it has:
  ∘ been frozen
  ∘ been dropped, damaged, or appears to be tampered with
  ∘ passed the expiration date (EXP)
Storing the WAINUA autoinjector
- Store the WAINUA autoinjector in the refrigerator between 36°F to 46°F (2°C to 8°C) in the original carton to protect from light. Do not freeze.
- If needed, the WAINUA autoinjector may be stored at room temperature up to 86°F (30°C) for up to a maximum of 6 weeks protected from light.
- If you do not use the WAINUA autoinjector within 6 weeks at room temperature, throw it away in an FDA-cleared sharps disposal container.
- Keep the autoinjector in the carton until ready to use.
  Keep your autoinjector and all medicines out of the sight and reach of children.

Overview of your WAINUA autoinjector

Do not remove the cap until just before you give the injection.

Do not touch the orange needle guard.

How does the WAINUA autoinjector work?

Make sure you read the entire instructions before uncapping and injecting.

The injection starts automatically when the orange needle guard is pushed against the skin.

The autoinjector must be held firmly against the skin to allow it to deliver the full dose of the medicine.

The injection is complete only when the orange plunger rod fills the viewing window (See “Overview of your WAINUA autoinjector”, After use).

Preparing to inject WAINUA using the autoinjector

Step 1 – Gather supplies for your injection

Step 2 – Wait 30 minutes

Keep the autoinjector in the original carton after removing it from the refrigerator and allow to come to room temperature for 30 minutes before injecting.

- Do not warm up in any other way. For example, do not warm it in a microwave or hot water, or near other heat sources.
- Keep it away from light or direct sunlight.

Step 3 – Remove from the carton and check the autoinjector and medicine

Check the autoinjector for damage.

- Do not use if damaged.

Check the expiration (EXP) date.

- Do not use if the expiration date has passed.

Check the liquid through the viewing window.

- It is normal to see small air bubbles in the liquid.
- The liquid should be clear and colorless to slightly yellow.
- Do not use if the liquid is cloudy, discolored, or contains large particles.

Injecting with your autoinjector

Step 4 – Choose an injection site

You or your caregiver can inject in the front of your thigh or your stomach (abdomen).

A caregiver may inject you in the back of your upper arm.

Do not try to inject yourself in the back of your upper arm.

For each injection, choose an injection site that is at least 1 inch (3 cm) away from where you last injected.

Do not inject:

- into the 2-inch (5-cm) area around your belly button
- where the skin is red, warm, tender, bruised, scaly, or hard
- into scars, damaged, discolored, or tattooed skin
- through clothing

Step 5 – Wash your hands and clean the injection site

Wash your hands well with soap and water.

Clean the injection site with an alcohol wipe or with soap and water. Let the site air dry.

- Do not touch the cleaned area before injecting.

Step 6 – Pull off the cap

Hold the autoinjector body with 1 hand, and carefully pull the cap straight off with your other hand. Do not twist it off. The orange needle guard is now exposed and the needle is hidden underneath.

- Throw away (dispose of) the cap.
- Do not touch the needle or push on the orange needle guard with your finger.
- Do not recap the autoinjector. This could cause the medicine to come out too soon or damage the autoinjector.

Step 7 – Inject WAINUA using the autoinjector

Inject the medicine using the autoinjector by following the steps in figures a, b, c and d.

When injecting, press and hold the autoinjector for 10 seconds until the orange plunger fills the viewing window. You may hear a first ‘click’ at the start of the injection and a second ‘click’ at the end of injection. This is normal.

Do not move or change the position of the autoinjector after the injection has started.

Position the autoinjector.

- Place the orange needle guard flat against your skin (90-degree angle).
- Make sure you can see the viewing window.

Step 8 – Check the viewing window

Check the viewing window to make sure all the medicine has been injected.

If the orange plunger rod does not fill the viewing window, you may not have received the full dose.

If this happens or if you have other concerns, contact your healthcare provider.

Step 9 – Check the injection site

There may be a small amount of blood or liquid where you injected. This is normal.

If needed, press a cotton ball or gauze on the area and apply a small bandage.

Step 10 – Throw away (dispose of) the used autoinjector

Put the used autoinjector in an FDA-cleared sharps disposal container right away after use.

Do not throw away the autoinjector in your household trash.

Disposal guidelines

If you do not have an FDA-cleared sharps disposal container, you may use a household container that is:

- made of a heavy-duty plastic,
- can be closed with a tight-fitting, puncture-resistant lid, without sharps being able to come out,
- upright and stable during use,
- leak-resistant, and
- properly labeled to warn of hazardous waste inside the container.

When your sharps disposal container is almost full, you will need to follow your community guidelines for the right way to dispose of your sharps disposal container. There may be state or local laws about how you should throw away used needles and autoinjectors. For more information about safe sharps disposal, and for specific information about sharps disposal in the area that you live in, go to the FDA's website at: http://www.fda.gov/safesharpsdisposal.

Do not throw away (dispose of) your used sharps disposal container in your household trash unless your community guidelines permit this.

Do not recycle your used sharps disposal container.

For more information, go to https://www.wainua.com or call 1-800-236-9933. If you still have questions, contact your healthcare provider.

Distributed by: AstraZeneca Pharmaceuticals LP, Wilmington, DE 19850

©AstraZeneca 2025

This Instructions for Use has been approved by the U.S. Food and Drug Administration. Revised: 12/2025

PACKAGE/LABEL PRINCIPAL DISPLAY PANEL

NDC 0310-9400-01 Rx only

WAINUA™ 45 mg/0.8 mL

(eplontersen) injection

for subcutaneous use

Each WAINUA autoinjector contains 45 mg eplontersen

(equivalent to 47 mg eplontersen sodium) in 0.8 mL of solution, for single-dose only.

Store refrigerated at 2°C to 8°C (36°F to 46°F) in the original carton protected from light.

Do not freeze. Do not expose to heat.

1 single-dose autoinjector

IONIS™ AstraZeneca